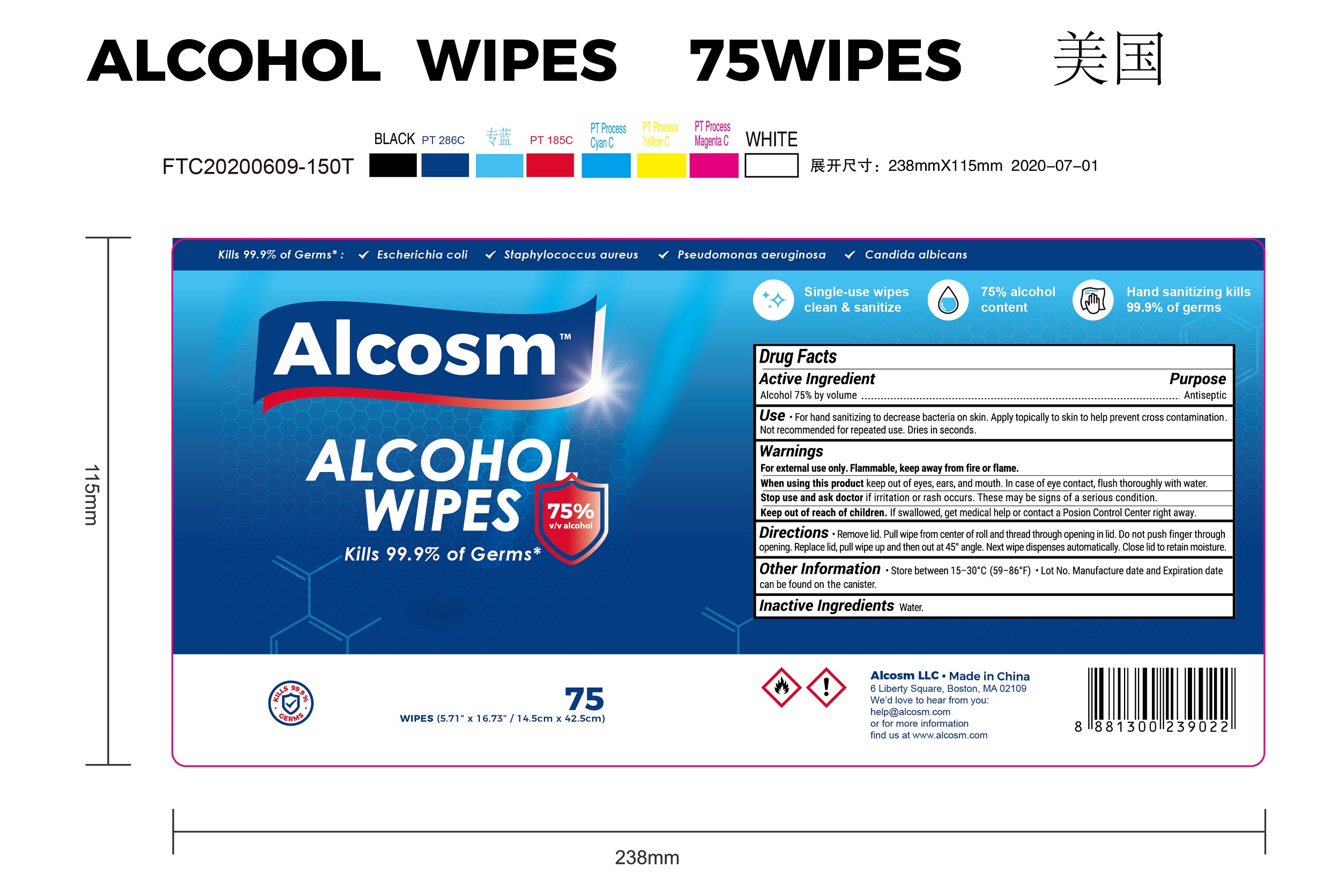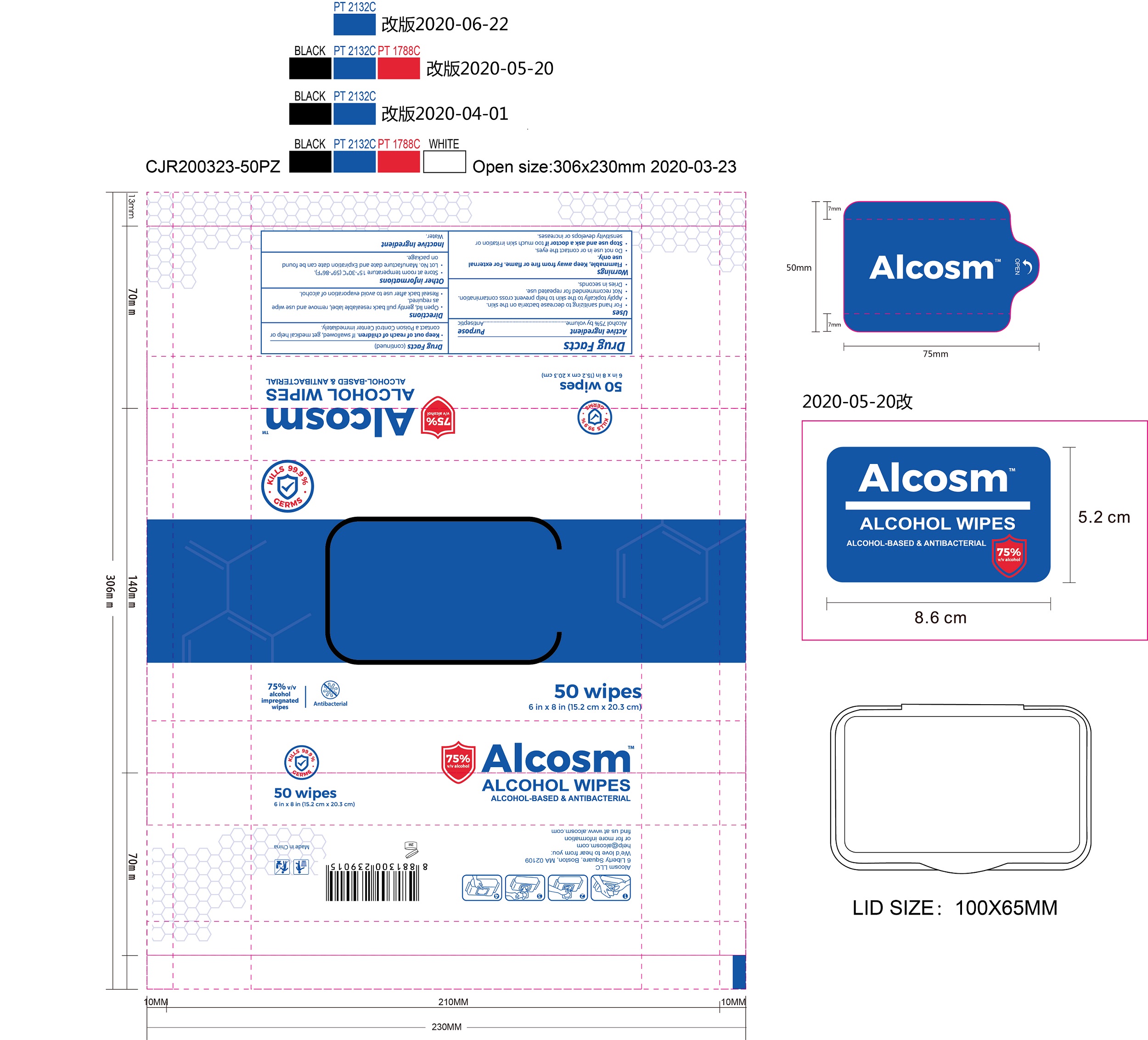 DRUG LABEL: Alcosm Alcohol Wipes
NDC: 75109-513 | Form: CLOTH
Manufacturer: Kangna (Zhejiang) Medical Supplies Co., Ltd.
Category: otc | Type: HUMAN OTC DRUG LABEL
Date: 20220114

ACTIVE INGREDIENTS: ALCOHOL 75 mL/100 mL
INACTIVE INGREDIENTS: WATER

75109-513 Alcosm alcohol wipes 75% Alcohol

Active Ingredient

Alcohol 75%

Purpose

Antiseptic

USE

For hand sanitizing to decrease bacteria on skin. Apply topically to skin to help prevent cross contamination.
Not recommended for repeated use. Dries in seconds.

Warning

For external use only. Flammable, keep away from fire or flame.
When using this product keep out of eyes, ears, and mouth. In case of eye contact, flush thoroughly with water.
Stop use and ask doctor if irritation or rash occurs. These may be signs of a serious condition.

●Keep out of reach of children. If swallowed, get medical
help or contact a Poison Control Center immediately.

Directions

Remove lid. Pull wipe from center of roll and thread through opening in lid. Do not push finger through
opening. Replace lid, pull wipe up and then out at 45° angle. Next wipe dispenses automatically. Close lid to retain moisture.

Inactive ingredients

Water